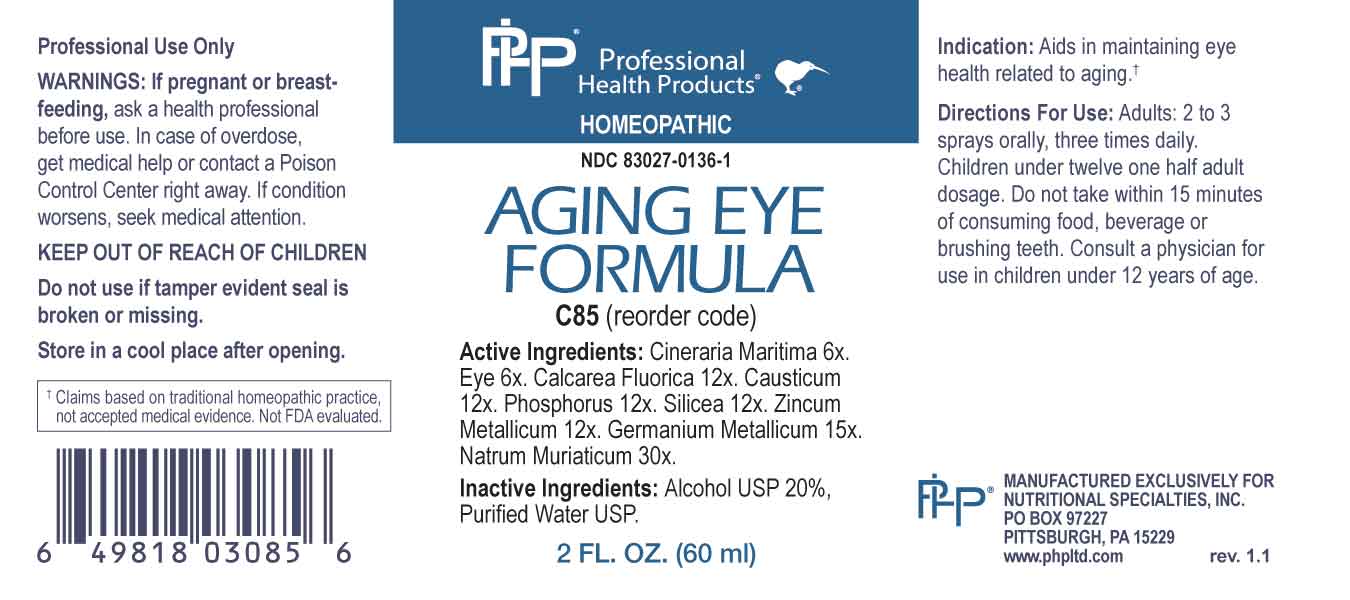 DRUG LABEL: Aging Eye Formula
NDC: 83027-0136 | Form: SPRAY
Manufacturer: Nutritional Specialties, Inc.
Category: homeopathic | Type: HUMAN OTC DRUG LABEL
Date: 20240523

ACTIVE INGREDIENTS: JACOBAEA MARITIMA WHOLE 6 [hp_X]/1 mL; SUS SCROFA EYE 6 [hp_X]/1 mL; CALCIUM FLUORIDE 12 [hp_X]/1 mL; CAUSTICUM 12 [hp_X]/1 mL; PHOSPHORUS 12 [hp_X]/1 mL; SILICON DIOXIDE 12 [hp_X]/1 mL; ZINC 12 [hp_X]/1 mL; GERMANIUM 15 [hp_X]/1 mL; SODIUM CHLORIDE 30 [hp_X]/1 mL
INACTIVE INGREDIENTS: WATER; ALCOHOL

DRUG FACTS:

ACTIVE INGREDIENTS:

Cineraria Maritima 6X, Eye 6X, Calcarea Fluorica 12X, Causticum 12X, Phosphorus 12X, Silicea 12X, Zincum Metallicum 12X, Germanium Metallicum 15X, Natrum Muriaticum 30X.

PURPOSE:

Aids in maintaining eye health related to aging.†

†Claims based on traditional homeopathic practice, not accepted medical evidence. Not FDA evaluated.

WARNINGS:

Professional Use Only

If pregnant or breast-feeding, ask a health professional before use.

In case of overdose, get medical help or contact a Poison Control Center right away.

If condition worsens, seek medical attention.

KEEP OUT OF REACH OF CHILDREN

Do not use if tamper evident seal is broken or missing.

Store in a cool place after opening

KEEP OUT OF REACH OF CHILDREN:

In case of overdose, get medical help or contact a Poison Control Center right away.

DIRECTIONS:

Adults: 2 to 3 sprays orally, three times daily. Children under twelve one half adult dosage. Do not take within 15 minutes of consuming food, beverage or brushing teeth. Consult a physician for use in children under 12 years of age.

INDICATIONS:

Aids in maintaining eye health related to aging.†

†Claims based on traditional homeopathic practice, not accepted medical evidence. Not FDA evaluated.

INACTIVE INGREDIENTS:

Alcohol USP 20%, Purified Water USP.

QUESTIONS:

MANUFACTURED EXCLUSIVELY FOR NUTRITIONAL SPECIALTIES, INC.

PO BOX 97227

PITTSBURG, PA 15229

www.phpltd.com

PACKAGE LABEL DISPLAY:

Professional

Health Products

HOMEOPATHIC

NDC 83027-0136-1

AGING EYE

FORMULA

2 FL. OZ (60 ml)